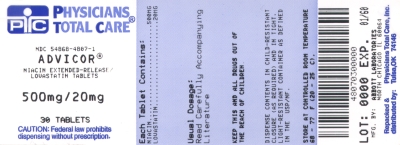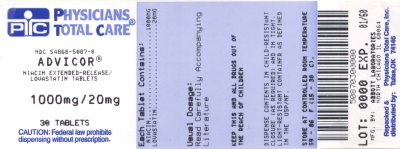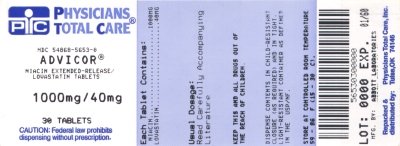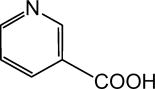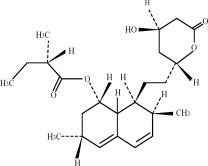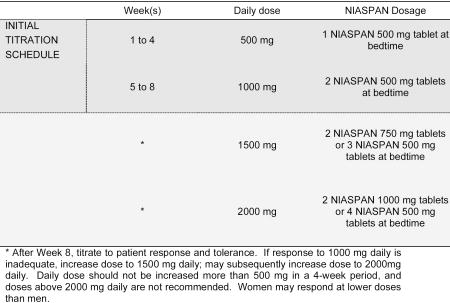 DRUG LABEL: Advicor
NDC: 54868-4807 | Form: TABLET, EXTENDED RELEASE
Manufacturer: Physicians Total Care, Inc.
Category: prescription | Type: HUMAN PRESCRIPTION DRUG LABEL
Date: 20121004

ACTIVE INGREDIENTS: NIACIN 500 mg/1 1; LOVASTATIN 20 mg/1 1
INACTIVE INGREDIENTS: POVIDONE; STEARIC ACID; POLYETHYLENE GLYCOLS; TITANIUM DIOXIDE; POLYSORBATE 80; FERRIC OXIDE RED; FERRIC OXIDE YELLOW; HYPROMELLOSES

Advicor®
(niacin extended-release/lovastatin tablets)

DESCRIPTION

ADVICOR® (niacin extended-release and lovastatin) is intended to facilitate the daily administration of its individual components, Niaspan® and lovastatin, when used together for the intended patient population (see INDICATIONS AND USAGE and DOSAGE AND ADMINISTRATION).

ADVICOR contains niacin extended-release and lovastatin in combination. Lovastatin, an inhibitor of 3-hydroxy-3-methylglutaryl-coenzyme A (HMG-CoA) reductase, and niacin are both lipid-altering agents.

Niacin is nicotinic acid, or 3-pyridinecarboxylic acid. Niacin is a white, nonhygroscopic crystalline powder that is very soluble in water, boiling ethanol and propylene glycol. It is insoluble in ethyl ether. The empirical formula of niacin is C6H5NO2 and its molecular weight is 123.11. Niacin has the following structural formula:

Lovastatin is [1S -[1(alpha)(R *), 3(alpha), 7(beta), 8(beta)(2S *, 4S *), 8a(beta)]]-1,2,3, 7,8,8a-hexahydro-3,7-dimethyl-8-[2-(tetrahydro-4-hydroxy-6-oxo-2H-pyran-2-yl) ethyl]-1-naphthalenyl 2-methylbutanoate. Lovastatin is a white, nonhygroscopic crystalline powder that is insoluble in water and sparingly soluble in ethanol, methanol, and acetonitrile. The empirical formula of lovastatin is C24H36O5 and its molecular weight is 404.55. Lovastatin has the following structural formula:

ADVICOR tablets contain the labeled amount of niacin and lovastatin and have the following inactive ingredients: hypromellose, povidone, stearic acid, polyethylene glycol, titanium dioxide, polysorbate 80.

The individual tablet strengths (expressed in terms of mg niacin/mg lovastatin) contain the following coloring agents:

ADVICOR 500 mg/20 mg - Iron Oxide Yellow, Iron Oxide Red.
ADVICOR 750 mg/20 mg - FD&C Yellow #6/Sunset Yellow FCF Aluminum Lake.
ADVICOR 1000 mg/20 mg - Iron Oxide Red, Iron Oxide Yellow, Iron Oxide Black.
ADVICOR 1000 mg/40 mg - Iron Oxide Red.

CLINICAL PHARMACOLOGY

A variety of clinical studies have demonstrated that elevated levels of total cholesterol (TC), low-density lipoprotein cholesterol (LDL-C), and apolipoprotein B-100 (Apo B) promote human atherosclerosis. Similarly, decreased levels of high-density lipoprotein cholesterol (HDL-C) are associated with the development of atherosclerosis. Epidemiological investigations have established that cardiovascular morbidity and mortality vary directly with the level of TC and LDL-C, and inversely with the level of HDL-C.

Cholesterol-enriched triglyceride-rich lipoproteins, including very low-density lipoproteins (VLDL), intermediate-density lipoproteins (IDL), and their remnants, can also promote atherosclerosis. Elevated plasma triglycerides (TG) are frequently found in a triad with low HDL-C levels and small LDL particles, as well as in association with non-lipid metabolic risk factors for coronary heart disease (CHD). As such, total plasma TG have not consistently been shown to be an independent risk factor for CHD.

As an adjunct to diet, the efficacy of niacin and lovastatin in improving lipid profiles (either individually, or in combination with each other, or niacin in combination with other statins) for the treatment of dyslipidemia has been well documented. The effect of combined therapy with niacin and lovastatin on cardiovascular morbidity and mortality has not been determined.

Effects on lipids

ADVICOR

ADVICOR reduces LDL-C, TC, and TG, and increases HDL-C due to the individual actions of niacin and lovastatin. The magnitude of individual lipid and lipoprotein responses may be influenced by the severity and type of underlying lipid abnormality.

Niacin

Niacin functions in the body after conversion to nicotinamide adenine dinucleotide (NAD) in the NAD coenzyme system. Niacin (but not nicotinamide) in gram doses reduces LDL-C, Apo B, Lp(a), TG, and TC, and increases HDL-C. The increase in HDL-C is associated with an increase in apolipoprotein A-I (Apo A-I) and a shift in the distribution of HDL subfractions. These shifts include an increase in the HDL2:HDL3 ratio, and an elevation in lipoprotein A-I (Lp A-I, an HDL-C particle containing only Apo A-I). In addition, preliminary reports suggest that niacin causes favorable LDL particle size transformations, although the clinical relevance of this effect is not yet clear.

Lovastatin

Lovastatin has been shown to reduce both normal and elevated LDL-C concentrations. Apo B also falls substantially during treatment with lovastatin. Since each LDL-C particle contains one molecule of Apo B, and since little Apo B is found in other lipoproteins, this strongly suggests that lovastatin does not merely cause cholesterol to be lost from LDL-C, but also reduces the concentration of circulating LDL particles. In addition, lovastatin can produce increases of variable magnitude in HDL-C, and modestly reduces VLDL-C and plasma TG. The effects of lovastatin on Lp(a), fibrinogen, and certain other independent biochemical risk markers for coronary heart disease are not well characterized.

Mechanism of Action

Niacin

The mechanism by which niacin alters lipid profiles is not completely understood and may involve several actions, including partial inhibition of release of free fatty acids from adipose tissue, and increased lipoprotein lipase activity (which may increase the rate of chylomicron triglyceride removal from plasma). Niacin decreases the rate of hepatic synthesis of VLDL-C and LDL-C, and does not appear to affect fecal excretion of fats, sterols, or bile acids.

Lovastatin

Lovastatin is a specific inhibitor of 3-hydroxy-3-methylglutaryl-coenzyme A (HMG-CoA) reductase, the enzyme that catalyzes the conversion of HMG-CoA to mevalonate. The conversion of HMG-CoA to mevalonate is an early step in the biosynthetic pathway for cholesterol. Lovastatin is a prodrug and has little, if any, activity until hydrolyzed to its active beta-hydroxyacid form, lovastatin acid. The mechanism of the LDL-lowering effect of lovastatin may involve both reduction of VLDL-C concentration and induction of the LDL receptor, leading to reduced production and/or increased catabolism of LDL-C.

Pharmacokinetics

Absorption and Bioavailability

ADVICOR

In single-dose studies of ADVICOR, rate and extent of niacin and lovastatin absorption were bioequivalent under fed conditions to that from NIASPAN® (niacin extended-release tablets) and Mevacor® (lovastatin) tablets, respectively. After administration of two ADVICOR 1000 mg/20 mg tablets, peak niacin concentrations averaged about 18 mcg/mL and occurred about 5 hours after dosing; about 72% of the niacin dose was absorbed according to the urinary excretion data. Peak lovastatin concentrations averaged about 11 ng/mL and occurred about 2 hours after dosing.

The extent of niacin absorption from ADVICOR was increased by administration with food. The administration of two ADVICOR 1000 mg/20 mg tablets under low-fat or high-fat conditions resulted in a 22 to 30% increase in niacin bioavailability relative to dosing under fasting conditions. Lovastatin bioavailability is affected by food. Lovastatin Cmax was increased 48% and 21% after a high- and a low-fat meal, respectively, but the lovastatin AUC was decreased 26% and 24% after a high- and a low-fat meal, respectively, compared to those under fasting conditions.

A relative bioavailability study results indicated that ADVICOR tablet strengths (i.e., two tablets of 500 mg/20 mg and one tablet of 1000 mg/40 mg) are not interchangeable.

Niacin

Due to extensive and saturable first-pass metabolism, niacin concentrations in the general circulation are dose dependent and highly variable. Peak steady-state niacin concentrations were 0.6, 4.9, and 15.5 mcg/mL after doses of 1000, 1500, and 2000 mg NIASPAN once daily (given as two 500 mg, two 750 mg, and two 1000 mg tablets, respectively).

Lovastatin

Lovastatin appears to be incompletely absorbed after oral administration. Because of extensive hepatic extraction, the amount of lovastatin reaching the systemic circulation as active inhibitors after oral administration is low (<5%) and shows considerable inter-individual variation. Peak concentrations of active and total inhibitors occur within 2 to 4 hours after Mevacor® administration.

Lovastatin absorption appears to be increased by at least 30% by grapefruit juice; however, the effect is dependent on the amount of grapefruit juice consumed and the interval between grapefruit juice and lovastatin ingestion. With a once-a-day dosing regimen, plasma concentrations of total inhibitors over a dosing interval achieved a steady-state between the second and third days of therapy and were about 1.5 times those following a single dose of Mevacor®.

Although the mechanism is not fully understood, cyclosporine has been shown to increase the AUC of HMG-CoA reductase inhibitors. The increase in AUC for lovastatin and lovastatin acid is presumably due, in part, to inhibition of CYP3A4.

Distribution

Niacin

Niacin is less than 20% bound to human serum proteins and distributes into milk. Studies using radiolabeled niacin in mice show that niacin and its metabolites concentrate in the liver, kidney, and adipose tissue.

Lovastatin

Both lovastatin and its beta-hydroxyacid metabolite are highly bound (>95%) to human plasma proteins. Distribution of lovastatin or its metabolites into human milk is unknown; however, lovastatin distributes into milk in rats. In animal studies, lovastatin concentrated in the liver, and crossed the blood-brain and placental barriers.

Metabolism

Niacin

Niacin undergoes rapid and extensive first-pass metabolism that is dose-rate specific and, at the doses used to treat dyslipidemia, saturable. In humans, one pathway is through a simple conjugation step with glycine to form nicotinuric acid (NUA). NUA is then excreted, although there may be a small amount of reversible metabolism back to niacin. The other pathway results in the formation of NAD. It is unclear whether nicotinamide is formed as a precursor to, or following the synthesis of, NAD. Nicotinamide is further metabolized to at least N-methylnicotinamide (MNA) and nicotinamide-N-oxide (NNO). MNA is further metabolized to two other compounds, N-methyl-2-pyridone-5-carboxamide (2PY) and N-methyl-4-pyridone-5-carboxamide (4PY). The formation of 2PY appears to predominate over 4PY in humans.

Lovastatin

Lovastatin undergoes extensive first-pass extraction and metabolism by cytochrome P450 3A4 in the liver, its primary site of action. The major active metabolites present in human plasma are the beta-hydroxyacid of lovastatin (lovastatin acid), its 6'-hydroxy derivative, and two additional metabolites.

Elimination

ADVICOR

Niacin is primarily excreted in urine mainly as metabolites. After a single dose of ADVICOR, at least 60% of the niacin dose was recovered in urine as unchanged niacin and its metabolites. The plasma half-life for lovastatin was about 4.5 hours in single-dose studies.

Niacin

The plasma half-life for niacin is about 20 to 48 minutes after oral administration and dependent on dose administered. Following multiple oral doses of NIASPAN, up to 12% of the dose was recovered in urine as unchanged niacin depending on dose administered. The ratio of metabolites recovered in the urine was also dependent on the dose administered.

Lovastatin

Lovastatin is excreted in urine and bile, based on studies of Mevacor®. Following an oral dose of radiolabeled lovastatin in man, 10% of the dose was excreted in urine and 83% in feces. The latter represents absorbed drug equivalents excreted in bile, as well as any unabsorbed drug.

Special Populations

Hepatic

No pharmacokinetic studies have been conducted in patients with hepatic insufficiency for either niacin or lovastatin (see WARNINGS, Liver Dysfunction).

Renal

No information is available on the pharmacokinetics of niacin in patients with renal insufficiency.

In a study of patients with severe renal insufficiency (creatinine clearance 10 to 30 mL/min), the plasma concentrations of total inhibitors after a single dose of lovastatin were approximately two-fold higher than those in healthy volunteers.

ADVICOR should be used with caution in patients with renal disease.

Gender

Plasma concentrations of niacin and metabolites after single- or multiple-dose administration of niacin are generally higher in women than in men, with the magnitude of the difference varying with dose and metabolite. Recovery of niacin and metabolites in urine, however, is generally similar for men and women, indicating similar absorption for both genders. The gender differences observed in plasma niacin and metabolite levels may be due to gender-specific differences in metabolic rate or volume of distribution. Data from clinical trials suggest that women have a greater hypolipidemic response than men at equivalent doses of NIASPAN and ADVICOR.

In a multiple-dose study, plasma concentrations of active and total HMG-CoA reductase inhibitors were 20 to 50% higher in women than in men. In two single-dose studies with ADVICOR, lovastatin concentrations were about 30% higher in women than men, and total HMG-CoA reductase inhibitor concentrations were about 20 to 25% greater in women.

In a multi-center, randomized, double-blind, active-comparator study in patients with Type IIa and IIb hyperlipidemia, ADVICOR was compared to single-agent treatment (NIASPAN and lovastatin). The treatment effects of ADVICOR compared to lovastatin and NIASPAN differed for males and females with a significantly larger treatment effect seen for females. The mean percent change from baseline at endpoint for LDL-C, TG, and HDL-C by gender are as follows (Table 1):

Table 1. Mean percent change from baseline at endpoint for LDL-C, HDL-C and TG by gender
 | ADVICOR 2000 mg/40 mg |  | NIASPAN 2000 mg |  | Lovastatin 40 mg
 | Women (n=22) | Men (n=30) | Women (n=28) | Men (n=28) | Women (n=21) | Men (n=38)
LDL-C | -47% | -34% | -12% | -9% | -31% | -31%
HDL-C | +33% | +24% | +22% | +15% | +3% | +7%
TG | -48% | -35% | -25% | -15% | -15% | -23%

Drug-drug Interactions

Table 2. The Effects of Other Drugs on Lovastatin Exposure When Both Were Co-administered
Drug | N | Dose of Co-administered Drug or Grapefruit Juice | Dosing of Lovastatin | AUC Ratio* (with / without co-administered drug)
Drug | N | Dose of Co-administered Drug or Grapefruit Juice | Dosing of Lovastatin | Lovastatin | Lovastatin Acid
Gemfibrozil | 11 | 600 mg BID for 3 days | 40 mg | 0.96 | 2.80
Itraconazole‡ | 12 | 200 mg QD for 4 days | 40 mg on Day 4 | > 36§ | 22
Itraconazole‡ | 10 | 100 mg QD for 4 days | 40 mg on Day 4 | > 14.8§ | 15.4
Grapefruit Juice¶ (high dose) | 10 | 200 mL of double-strength TID# | 80 mg single dose | 15.3 | 5.0
Grapefruit Juice¶ (low dose) | 16 | 8 oz (about 250 mL) of single-strengthÞ for 4 days | 40 mg single dose | 1.94 | 1.57
Cyclosporine | 16 | Not describedß | 10 mg QD for 10 days | 5- to 8-fold | NDà
 | Number of Subjects | Dosing of Coadministered Drug or Grapefruit Juice | Dosing of Lovastatin | AUC Ratio* (with / without co-administered drug) No Effect = 1.00
 |  |  |  | Total Lovastatin Acid è
Diltiazem | 10 | 120 mg BID for 14 days | 20 mg | 3.57è
* Results based on a chemical assay.
† Lovastatin acid refers to the β-hydroxyacid of lovastatin.
‡ The mean total AUC of lovastatin without itraconazole phase could not be determined accurately. Results could be representative of strong CYP3A4 inhibitors such as ketoconazole, posaconazole, clarithromycin, telithromycin, HIV protease inhibitors, and nefazodone.
§ Estimated minimum change.
¶ The effect of amounts of grapefruit juice between those used in these two studies on lovastatin pharmacokinetics has not been studied.
# Double-strength: one can of frozen concentrate diluted with one can of water. Grapefruit juice was administered TID for 2 days, and 200 mL together with single dose lovastatin and 30 and 90 minutes following single dose lovastatin on Day 3.
Þ Single-strength: one can of frozen concentrate diluted with 3 cans of water. Grapefruit juice was administered with breakfast for 3 days, and lovastatin was administered in the evening on Day 3.
ß Cyclosporine-treated patients with psoriasis or post kidney or heart transplant patients with stable graft function, transplanted at least 9 months prior to study.
à ND = Analyte not determined.
è Lactone converted to acid by hydrolysis prior to analysis. Figure represents total unmetabolized acid and lactone.

Clinical Studies

In a multi-center, randomized, double-blind, parallel, 28-week, active-comparator study in patients with Type IIa and IIb hyperlipidemia, ADVICOR was compared to each of its components (NIASPAN and lovastatin). Using a forced dose-escalation study design, patients received each dose for at least 4 weeks. Patients randomized to treatment with ADVICOR initially received 500 mg/20 mg. The dose was increased at 4-week intervals to a maximum of 1000 mg/20 mg in one-half of the patients and 2000 mg/40 mg in the other half. The NIASPAN monotherapy group underwent a similar titration from 500 mg to 2000 mg. The patients randomized to lovastatin monotherapy received 20 mg for 12 weeks titrated to 40 mg for up to 16 weeks. Up to a third of the patients randomized to ADVICOR or NIASPAN discontinued prior to Week 28. In this study, ADVICOR decreased LDL-C, TG and Lp(a), and increased HDL-C in a dose-dependent fashion (Tables 3, 4, 5 and 6 below). Results from this study for LDL-C mean percent change from baseline (the primary efficacy variable) showed that:

1. LDL-lowering with ADVICOR was significantly greater than that achieved with lovastatin 40 mg only after 28 weeks of titration to a dose of 2000 mg/40 mg (p<.0001)
2. ADVICOR at doses of 1000 mg/20 mg or higher achieved greater LDL-lowering than NIASPAN (p<.0001) The LDL-C results are summarized in Table 3.

Table 3. LDL-C mean percent change from baseline
Week | ADVICOR |  |  | NIASPAN |  |  | Lovastatin
 | n* | Dose (mg/mg) | LDL | n* | Dose (mg) | LDL | n* | Dose (mg) | LDL
Baseline | 57 | - | 190.9 mg/dL | 61 | - | 189.7 mg/dL | 61 | - | 185.6 mg/dL
12 | 47 | 1000/20 | -30% | 46 | 1000 | -3% | 56 | 20 | -29%
16 | 45 | 1000/40 | -36% | 44 | 1000 | -6% | 56 | 40 | -31%
20 | 42 | 1500/40 | -37% | 43 | 1500 | -12% | 54 | 40 | -34%
28 | 42 | 2000/40 | -42% | 41 | 2000 | -14% | 53 | 40 | -32%
*n = number of patients remaining in the trial at each timepoint

ADVICOR achieved significantly greater HDL-raising compared to lovastatin and NIASPAN monotherapy at all doses (Table 4).

Table 4. HDL-C mean percent change from baseline
Week | ADVICOR |  |  | NIASPAN |  |  | Lovastatin
 | n* | Dose (mg/mg) | HDL | n* | Dose (mg) | HDL | n* | Dose (mg) | HDL
Baseline | 57 | - | 45 mg/dL | 61 | - | 47 mg/dL | 61 | - | 43 mg/dL
12 | 47 | 1000/20 | +20% | 46 | 1000 | +14% | 56 | 20 | +3%
16 | 45 | 1000/40 | +20% | 44 | 1000 | +15% | 56 | 40 | +5%
20 | 42 | 1500/40 | +27% | 43 | 1500 | +22% | 54 | 40 | +6%
28 | 42 | 2000/40 | +30% | 41 | 2000 | +24% | 53 | 40 | +6%
*n = number of patients remaining in the trial at each timepoint

In addition, ADVICOR achieved significantly greater TG-lowering at doses of 1000 mg/20 mg or greater compared to lovastatin and NIASPAN monotherapy (Table 5).

Table 5. TG median percent change from baseline
Week | ADVICOR |  |  | NIASPAN |  |  | Lovastatin
 | n* | Dose (mg/mg) | TG | n* | Dose (mg) | TG | n* | Dose (mg) | TG
Baseline | 57 | - | 174 mg/dL | 61 | - | 186 mg/dL | 61 | - | 171 mg/dL
12 | 47 | 1000/20 | -32% | 46 | 1000 | -22% | 56 | 20 | -20%
16 | 45 | 1000/40 | -39% | 44 | 1000 | -23% | 56 | 40 | -17%
20 | 42 | 1500/40 | -44% | 43 | 1500 | -31% | 54 | 40 | -21%
28 | 42 | 2000/40 | -44% | 41 | 2000 | -31% | 53 | 40 | -20%
*n = number of patients remaining in the trial at each timepoint

The Lp(a) lowering effects of ADVICOR and NIASPAN were similar, and both were superior to lovastatin (Table 6). The independent effect of lowering Lp(a) with NIASPAN or ADVICOR on the risk of coronary and cardiovascular morbidity and mortality has not been determined.

Table 6. Lp(a) median percent change from baseline
Week | ADVICOR |  |  | NIASPAN |  |  | Lovastatin
 | n* | Dose (mg/mg) | Lp(a) | n* | Dose (mg) | Lp(a) | n* | Dose (mg) | Lp(a)
Baseline | 57 | - | 34 mg/dL | 61 | - | 41 mg/dL | 60 | - | 42 mg/dL
12 | 47 | 1000/20 | -9% | 46 | 1000 | -8% | 55 | 20 | +8%
16 | 45 | 1000/40 | -9% | 44 | 1000 | -12% | 55 | 40 | +8%
20 | 42 | 1500/40 | -17% | 43 | 1500 | -22% | 53 | 40 | +6%
28 | 42 | 2000/40 | -22% | 41 | 2000 | -32% | 52 | 40 | 0%
*n = number of patients remaining in the trial at each timepoint

ADVICOR Long-Term Study

A total of 814 patients were enrolled in a long-term (52-week), open-label, single-arm study of ADVICOR. Patients were force dose-titrated to 2000 mg/40 mg over 16 weeks. After titration, patients were maintained on the maximum tolerated dose of ADVICOR for a total of 52 weeks. Five hundred-fifty (550) patients (68%) completed the study, and fifty-six percent (56%) of all patients were able to maintain a dose of 2000 mg/40 mg for the 52 weeks of treatment. The lipid-altering effects of ADVICOR peaked after 4 weeks on the maximum tolerated dose, and were maintained for the duration of treatment. These effects were comparable to what was observed in the double-blind study of ADVICOR (Tables 3-5).

INDICATIONS AND USAGE

Therapy with lipid-altering agents should be only one component of multiple risk-factor intervention in individuals at significantly increased risk for atherosclerotic vascular disease due to hypercholesterolemia. Drug therapy is indicated as an adjunct to diet when the response to a diet restricted in saturated fat and cholesterol and other nonpharmacologic measures alone has been inadequate (see also Table 8 and the NCEP treatment guidelines^1).

ADVICOR

ADVICOR (niacin extended-release and lovastatin) is indicated for use when treatment with both NIASPAN and lovastatin is appropriate. As described in the labeling for Niaspan and lovastatin below, the components of ADVICOR are both indicated for the treatment of hypercholesterolemia. Patients receiving treatment with ADVICOR should be on a standard cholesterol-lowering diet and should continue on this diet during treatment.

NIASPAN (niacin extended-release)

Hypercholesterolemia

NIASPAN is indicated as an adjunct to diet for reduction of elevated TC, LDL-C, Apo B and TG levels, and to increase HDL-C in patients with primary hypercholesterolemia (heterozygous familial and nonfamilial) and mixed dyslipidemia (Table 7), when the response to an appropriate diet has been inadequate.

Secondary Prevention of Cardiovascular Events

In patients with a history of myocardial infarction and hypercholesterolemia, niacin is indicated to reduce the risk of recurrent nonfatal myocardial infarction.

Hypertriglyceridemia

Niacin is also indicated as adjunctive therapy for treatment of adult patients with very high serum triglyceride levels (Table 7) who present a risk of pancreatitis and who do not respond adequately to a determined dietary effort to control them. Such patients typically have serum TG levels over 2000 mg/dL and have elevations of VLDL-C as well as fasting chylomicrons (Table 7). Patients who consistently have total serum or plasma TG below 1000 mg/dL are unlikely to develop pancreatitis. Therapy with niacin may be considered for those patients with TG elevations between 1000 and 2000 mg/dL who have a history of pancreatitis or of recurrent abdominal pain typical of pancreatitis. Some patients with TG under 1000 mg/dL may, through dietary or alcohol indiscretion, convert to a pattern with massive TG elevations accompanying fasting chylomicronemia, but the influence of niacin therapy on risk of pancreatitis in such situations has not been adequately studied. Drug therapy is not indicated for patients with hyperlipoproteinemia, who have elevations of chylomicrons and plasma TG, but who have normal levels of VLDL-C.

Lovastatin

Hypercholesterolemia

Lovastatin is indicated as an adjunct to diet for the reduction of elevated TC and LDL-C levels in patients with primary hypercholesterolemia (Table 7), when the response to diet restricted in saturated fat and cholesterol and to other nonpharmacological measures alone has been inadequate.

Primary Prevention of Cardiovascular Events

In individuals without symptomatic cardiovascular disease, average to moderately elevated TC and LDL-C, and below average HDL-C, lovastatin is indicated to reduce the risk of:

- Myocardial infarction
- Unstable angina
- Coronary revascularization procedures

Secondary Prevention of Cardiovascular Events

Lovastatin is also indicated to slow the progression of coronary atherosclerosis in patients with coronary heart disease as part of a treatment strategy to lower TC and LDL-C to target levels.

The National Cholesterol Education Program (NCEP) Treatment Guidelines are summarized below:

Table 7. Classification of Hyperlipoproteinemias
Type | Lipoproteins Elevated | Lipid Elevations
I (rare) | Chylomicrons | Major |  | Minor
IIa | LDL | TG |  | ↑→TC
IIb | LDL,VLDL | TC |  | -
III (rare) | IDL | TC |  | TG
IV | VLDL | TC/TG |  | -
V (rare) | Chylomicrons, VLDL | TG |  | ↑→TC
TC = total cholesterol; TG = triglycerides; LDL = low-density lipoprotein; VLDL = very low-density lipoprotein; IDL = intermediate-density lipoprotein ↑→ = increased or no change

General Recommendations

Prior to initiating therapy with a lipid-lowering agent, secondary causes for hypercholesterolemia (e.g., poorly controlled diabetes mellitus, hypothyroidism, nephrotic syndrome, dysproteinemias, obstructive liver disease, other drug therapy, alcoholism) should be excluded, and a lipid profile performed to measure TC, HDL-C, and TG. For patients with TG < 400 mg/dL, LDL-C can be estimated using the following equation:

LDL-C = TC - [(0.20 x TG) + HDL-C]

For TG levels > 400 mg/dL, this equation is less accurate and LDL-C concentrations should be determined by ultracentrifugation. Lipid determinations should be performed at intervals of no less than 4 weeks and dosage adjusted according to the patient's response to therapy. The NCEP Treatment Guidelines are summarized in Table 8.

Table 8. NCEP Treatment Guidelines: LDL-C Goals and Cutpoints for Therapeutic Lifestyle Changes and Drug Therapy in Different Risk Categories
Risk Category | LDL Goal (mg/dL) | LDL Level at Which to Initiate Therapeutic Lifestyle Changes (mg/dL) | LDL Level at Which to Consider Drug Therapy (mg/dL)
CHD† or CHD risk equivalents (10-year risk >20%) | <100 | ≥ 100 | ≥ 130 (100-129:drug optional) ††
2+ Risk factors (10-year risk ≤20%) | <130 | ≥ 130 | 10-year risk 10%-20%: ≥ 130 10-year risk <10%: ≥ 160
0-1 Risk factor ††† | <160 | ≥ 160 | ≥ 190 (160-189:LDL-lowering drug optional)
† CHD, coronary heart disease
†† Some authorities recommend use of LDL-lowering drugs in this category if an LDL-C level of <100 mg/dL cannot be achieved by therapeutic lifestyle changes. Others prefer use of drugs that primarily modify triglycerides and HDL-C, e.g., nicotinic acid or fibrate. Clinical judgement also may call for deferring drug therapy in this subcategory.
††† Almost all people with 0-1 risk factor have 10-year risk <10%; thus, 10-year risk assessment in people with 0-1 risk factor is not necessary.

After the LDL-C goal has been achieved, if the TG is still ≥200 mg/dL, non-HDL-C (TC minus HDL-C) becomes a secondary target of therapy. Non-HDL-C goals are set 30 mg/dL higher than LDL-C goals for each risk category.

CONTRAINDICATIONS

ADVICOR is contraindicated in patients with a known hypersensitivity to niacin, lovastatin or any component of this medication, active liver disease or unexplained persistent elevations in serum transaminases (see WARNINGS), active peptic ulcer disease, or arterial bleeding.

Concomitant administration with strong CYP3A4 inhibitors (e.g., itraconazole, ketoconazole, posaconazole, HIV protease inhibitors, boceprevir, telaprevir, erythromycin, clarithromycin, telithromycin and nefazodone) (see WARNINGS, Myopathy/Rhabdomyolysis).

Pregnancy and lactation - Atherosclerosis is a chronic process and the discontinuation of lipid-lowering drugs during pregnancy should have little impact on the outcome of long-term therapy of primary hypercholesterolemia. Moreover, cholesterol and other products of the cholesterol biosynthesis pathway are essential components for fetal development, including synthesis of steroids and cell membranes. Because of the ability of inhibitors of HMG-CoA reductase, such as lovastatin, to decrease the synthesis of cholesterol and possibly other products of the cholesterol biosynthesis pathway, ADVICOR is contraindicated in women who are pregnant and in lactating mothers. ADVICOR may cause fetal harm when administered to pregnant women. ADVICOR should be administered to women of childbearing age only when such patients are highly unlikely to conceive. If the patient becomes pregnant while taking this drug, ADVICOR should be discontinued immediately and the patient should be apprised of the potential hazard to the fetus (see PRECAUTIONS, Pregnancy).

WARNINGS

ADVICOR should not be substituted for equivalent doses of immediate-release (crystalline) niacin. For patients switching from immediate-release niacin to NIASPAN, therapy with NIASPAN should be initiated with low doses (i.e., 500 mg once daily at bedtime) and the NIASPAN dose should then be titrated to the desired therapeutic response (see DOSAGE AND ADMINISTRATION).

Liver Dysfunction

Cases of severe hepatic toxicity, including fulminant hepatic necrosis, have occurred in patients who have substituted sustained-release (modified-release, timed-release) niacin products for immediate-release (crystalline) niacin at equivalent doses.

ADVICOR should be used with caution in patients who consume substantial quantities of alcohol and/or have a past history of liver disease. Active liver disease or unexplained transaminase elevations are contraindications to the use of ADVICOR.

Niacin preparations and lovastatin preparations have been associated with abnormal liver tests. In studies using NIASPAN alone, 0.8% of patients were discontinued for transaminase elevations. In studies using lovastatin alone, 0.2% of patients were discontinued for transaminase elevations.^2 In three safety and efficacy studies involving titration to final daily ADVICOR doses ranging from 500 mg/10 mg to 2500 mg/40 mg, ten of 1028 patients (1.0%) experienced reversible elevations in AST/ALT to more than 3 times the upper limit of normal (ULN). Three of ten elevations occurred at doses outside the recommended dosing limit of 2000 mg/40 mg; no patient receiving 1000 mg/20 mg had 3-fold elevations in AST/ALT.

In clinical studies with ADVICOR, elevations in transaminases did not appear to be related to treatment duration; elevations in AST and ALT levels did appear to be dose related. Transaminase elevations were reversible upon discontinuation of ADVICOR.

It is recommended that liver enzyme tests be obtained prior to initiating therapy with ADVICOR and repeated as clinically indicated.

There have been rare postmarketing reports of fatal and non-fatal hepatic failure in patients taking statins, including lovastatin. If serious liver injury with clinical symptoms and/or hyperbilirubinemia or jaundice occurs during treatment with ADVICOR, promptly interrupt therapy. If an alternate etiology is not found do not restart ADVICOR.

Myopathy/Rhabdomyolysis

Lovastatin and other inhibitors of HMG-CoA reductase occasionally cause myopathy, which is manifested as muscle pain or weakness associated with grossly elevated creatine kinase (> 10 times ULN). Rhabdomyolysis, with or without acute renal failure secondary to myoglobinuria, has been reported rarely and can occur at any time. In a large, long-term, clinical safety and efficacy study (the EXCEL study)^3,4 with lovastatin, myopathy occurred in up to 0.2% of patients treated with lovastatin 20 to 80 mg for up to 2 years. When drug treatment was interrupted or discontinued in these patients, muscle symptoms and creatine kinase (CK) increases promptly resolved. The risk of myopathy is increased by concomitant therapy with certain drugs, some of which were excluded by the EXCEL study design.

The risk of myopathy/rhabdomyolysis is increased by concomitant use of lovastatin with the following:

Strong inhibitors of CYP3A4: The risk of myopathy appears to be increased by high levels of HMG-CoA reductase inhibitory activity in plasma. Lovastatin is metabolized by the cytochrome P450 isoform 3A4. Certain drugs which share this metabolic pathway can raise the plasma levels of lovastatin and may increase the risk of myopathy. These include itraconazole, ketoconazole, and posaconazole, the macrolide antibiotics erythromycin and clarithromycin, and the ketolide antibiotic telithromycin, HIV protease inhibitors, boceprevir, telaprevir, the antidepressant nefazodone, or large quantities of grapefruit juice (>1 quart daily). Combination of these drugs with lovastatin is contraindicated. If treatment with itraconazole, ketoconazole, erythromycin, clarithromycin or telithromycin is unavoidable, therapy with lovastatin should be suspended during the course of treatment.

Although not studied clinically, voriconazole has been shown to inhibit lovastatin metabolism in vitro (human liver microsomes). Therefore, voriconazole is likely to increase the plasma concentration of lovastatin. It is recommended that dose adjustment of lovastatin be considered during coadministration. Increased lovastatin concentration in plasma has been associated with an increased risk of myopathy/rhabdomyolysis.

Gemfibrozil: The combined use of lovastatin with gemfibrozil should be avoided.

Other fibrates: Caution should be used when prescribing other fibrates with lovastatin, as these agents can cause myopathy when given alone. The benefit of further alterations in lipid levels by the combined use of lovastatin with other fibrates should be carefully weighed against the potential risks of this combination.

Cyclosporine: The use of lovastatin with cyclosporine should be avoided.

Danazol, diltiazem or verapamil with higher doses of lovastatin: In patients taking concomitant danazol, diltiazem or verapamil, the dose of lovastatin should not exceed 20 mg (see DOSAGE AND ADMINISTRATION), as the risk of myopathy increases at higher doses. The benefits of the use of lovastatin in patients receiving danazol, diltiazem, or verapamil should be carefully weighed against the risks of these combinations.

Amiodarone: In patients taking concomitant amiodarone, the dose of lovastatin should not exceed 40 mg (see DOSAGE AND ADMINISTRATION), as the risk of myopathy increases at higher doses.

Colchicine: Cases of myopathy, including rhabdomyolysis, have been reported with lovastatin coadministered with colchicine, and caution should be exercised when prescribing lovastatin with colchicine.

Ranolazine: The risk of myopathy, including rhabdomyolysis, may be increased by concomitant administration of ranolazine. Dose adjustment of lovastatin may be considered during co-administration with ranolazine.

Prescribing recommendations for interacting agents are summarized in Table 9.

Table 9
Drug Interactions Associated with Increased
Risk of Myopathy/Rhabdomyolysis
Interacting Agents | Prescribing Recommendations
Strong CYP3A4 inhibitors, e.g.: Ketoconazole Itraconazole Posaconazole Erythromycin Clarithromycin Telithromycin HIV protease inhibitors Boceprevir Telaprevir Nefazodone | Contraindicated with lovastatin
Gemfibrozil Cyclosporine | Avoid with lovastatin
Danazol Diltiazem Verapamil | Do not exceed 20 mg lovastatin daily
Amiodarone | Do not exceed 40 mg lovastatin daily
Grapefruit juice | Avoid large quantities of grapefruit juice (>1 quart daily)

ADVICOR

Myopathy and/or rhabdomyolysis have been reported when lovastatin is used in combination with lipid-altering doses (≥1g/day) of niacin. Physicians contemplating the use of ADVICOR, a combination of lovastatin and niacin, should weigh the potential benefits and risks, and should carefully monitor patients for any signs and symptoms of muscle pain, tenderness, or weakness, particularly during the initial month of treatment or during any period of upward dosage titration of either drug. Periodic CK determinations may be considered in such situations, but there is no assurance that such monitoring will prevent myopathy.

In clinical studies, no cases of rhabdomyolysis and one suspected case of myopathy have been reported in 1079 patients who were treated with ADVICOR at doses up to 2000 mg/40 mg for periods up to 2 years.

Patients starting therapy with ADVICOR should be advised of the risk of myopathy, and told to report promptly unexplained muscle pain, tenderness, or weakness. A CK level above 10 times ULN in a patient with unexplained muscle symptoms indicates myopathy. ADVICOR therapy should be discontinued if myopathy is diagnosed or suspected.

In patients with complicated medical histories predisposing to rhabdomyolysis, such as preexisting renal insufficiency, dose escalation requires caution. ADVICOR therapy should be discontinued if markedly elevated CPK levels occur or myopathy is diagnosed or suspected. ADVICOR therapy should also be temporarily withheld in any patient experiencing an acute or serious condition predisposing to the development of renal failure secondary to rhabdomyolysis, e.g., sepsis; hypotension; major surgery; trauma; severe metabolic, endocrine, or electrolyte disorders; or uncontrolled epilepsy.

PRECAUTIONS

General

Before instituting therapy with a lipid-altering medication, an attempt should be made to control dyslipidemia with appropriate diet, exercise, and weight reduction in obese patients, and to treat other underlying medical problems (see INDICATIONS AND USAGE).

Patients with a past history of jaundice, hepatobiliary disease, or peptic ulcer should be observed closely during ADVICOR therapy. Frequent monitoring of liver function tests and blood glucose should be performed to ascertain that the drug is producing no adverse effects on these organ systems.

Diabetic patients may experience a dose-related rise in fasting blood sugar (FBS). In three clinical studies, which included 1028 patients exposed to ADVICOR (6 to 22% of whom had diabetes type II at baseline), increases in FBS above normal occurred in 46 to 65% of patients at any time during study treatment with ADVICOR. Fourteen patients (1.4%) were discontinued from study treatment: 3 patients for worsening diabetes, 10 patients for hyperglycemia and 1 patient for a new diagnosis of diabetes. In the studies in which lovastatin and NIASPAN were used as active controls, 24 to 41% of patients receiving lovastatin and 43 to 58% of patients receiving NIASPAN also had increases in FBS above normal. One patient (1.1%) receiving lovastatin was discontinued for hyperglycemia. Diabetic or potentially diabetic patients should be observed closely during treatment with ADVICOR, and adjustment of diet and/or hypoglycemic therapy may be necessary.

In one long-term study of 106 patients treated with ADVICOR, elevations in prothrombin time (PT) >3 times ULN occurred in 2 patients (2%) during study drug treatment. In a long-term study of 814 patients treated with ADVICOR, 7 patients were noted to have platelet counts <100,000 during study drug treatment. Four of these patients were discontinued, and one patient with a platelet count <100,000 had prolonged bleeding after a tooth extraction. Prior studies have shown that NIASPAN can be associated with dose-related reductions in platelet count (mean of -11% with 2000 mg) and increases of PT (mean of approximately +4%). Accordingly, patients undergoing surgery should be carefully evaluated. In controlled studies, ADVICOR has been associated with small but statistically significant dose-related reductions in phosphorus levels (mean of -10% with 2000 mg/40 mg). Phosphorus levels should be monitored periodically in patients at risk for hypophosphatemia. In clinical studies with ADVICOR, hypophosphatemia was more common in males than in females. The clinical relevance of hypophosphatemia in this population is not known.

Niacin

Caution should also be used when ADVICOR is used in patients with unstable angina or in the acute phase of MI, particularly when such patients are also receiving vasoactive drugs such as nitrates, calcium channel blockers, or adrenergic blocking agents.

Elevated uric acid levels have occurred with niacin therapy; therefore, in patients predisposed to gout, niacin therapy should be used with caution. Niacin is rapidly metabolized by the liver, and excreted through the kidneys. ADVICOR is contraindicated in patients with significant or unexplained hepatic dysfunction (see CONTRAINDICATIONS and WARNINGS) and should be used with caution in patients with renal dysfunction.

Lovastatin

Lovastatin may elevate creatine phosphokinase and transaminase levels (see WARNINGS and ADVERSE REACTIONS). This should be considered in the differential diagnosis of chest pain in a patient on therapy with lovastatin.

Endocrine function - Increases in HbA1c and fasting serum glucose levels have been reported with HMG-CoA reductase inhibitors, including lovastatin.

HMG-CoA reductase inhibitors interfere with cholesterol synthesis and as such might theoretically blunt adrenal and/or gonadal steroid production. Results of clinical studies with drugs in this class have been inconsistent with regard to drug effects on basal and reserve steroid levels. However, clinical studies have shown that lovastatin does not reduce basal plasma cortisol concentration or impair adrenal reserve, and does not reduce basal plasma testosterone concentration. Another HMG-CoA reductase inhibitor has been shown to reduce the plasma testosterone response to human chorionic gonadotropin (HCG). In the same study, the mean testosterone response to HCG was slightly but not significantly reduced after treatment with lovastatin 40 mg daily for 16 weeks in 21 men. The effects of HMG-CoA reductase inhibitors on male fertility have not been studied in adequate numbers of male patients. The effects, if any, on the pituitary-gonadal axis in premenopausal women are unknown. Patients treated with lovastatin who develop clinical evidence of endocrine dysfunction should be evaluated appropriately. Caution should also be exercised if an HMG-CoA reductase inhibitor or other agent used to lower cholesterol levels is administered to patients also receiving other drugs (e.g., spironolactone, cimetidine) that may decrease the levels or activity of endogenous steroid hormones.

CNS toxicity - Lovastatin produced optic nerve degeneration (Wallerian degeneration of retinogeniculate fibers) in clinically normal dogs in a dose-dependent fashion starting at 60 mg/kg/day, a dose that produced mean plasma drug levels about 30 times higher than the mean drug level in humans taking the highest recommended dose (as measured by total enzyme inhibitory activity). Vestibulocochlear Wallerian-like degeneration and retinal ganglion cell chromatolysis were also seen in dogs treated for 14 weeks at 180 mg/kg/day, a dose which resulted in a mean plasma drug level (Cmax) similar to that seen with the 60 mg/kg/day dose.

CNS vascular lesions, characterized by perivascular hemorrhage and edema, mononuclear cell infiltration of perivascular spaces, perivascular fibrin deposits and necrosis of small vessels, were seen in dogs treated with lovastatin at a dose of 180 mg/kg/day, a dose which produced plasma drug levels (Cmax) which were about 30 times higher than the mean values in humans taking 80 mg/day.

Similar optic nerve and CNS vascular lesions have been observed with other drugs of this class.

Cataracts were seen in dogs treated with lovastatin for 11 and 28 weeks at 180 mg/kg/day and 1 year at 60mg/kg/day.

Information for Patients

Patients should be advised of the following:

- to report promptly unexplained muscle pain, tenderness, or weakness (see WARNINGS, Myopathy/Rhabdomyolysis);
- to report promptly any symptoms that may indicate liver injury, including fatigue, anorexia, right upper abdominal discomfort, dark urine or jaundice (see WARNINGS, Liver Dysfunction);
- to take ADVICOR at bedtime, with a low-fat snack. Administration on an empty stomach is not recommended;
- to carefully follow the prescribed dosing regimen (see DOSAGE AND ADMINISTRATION);
- that flushing is a common side effect of niacin therapy that usually subsides after several weeks of consistent niacin use. Flushing may last for several hours after dosing, may vary in severity, and will, by taking ADVICOR at bedtime, most likely occur during sleep. If awakened by flushing, especially if taking antihypertensives, rise slowly to minimize the potential for dizziness and/or syncope;
- that taking aspirin (up to approximately 30 minutes before taking ADVICOR) may minimize flushing;
- to avoid ingestion of alcohol, hot beverages and spicy foods around the time of ADVICOR administration, to minimize flushing;
- should not be administered with grapefruit juice;
- that if ADVICOR therapy is discontinued for an extended length of time, their physician should be contacted prior to re-starting therapy; re-titration is recommended (see DOSAGE AND ADMINISTRATION);
- to notify their physician if they are taking vitamins or other nutritional supplements containing niacin or related compounds such as nicotinamide (see Drug Interactions);
- to notify their physician if symptoms of dizziness occur;
- if diabetic, to notify their physician of changes in blood glucose;
- that ADVICOR tablets should not be broken, crushed, or chewed, but should be swallowed whole.

Drug Interactions

Niacin

Antihypertensive Therapy - Niacin may potentiate the effects of ganglionic blocking agents and vasoactive drugs resulting in postural hypotension.

Aspirin - Concomitant aspirin may decrease the metabolic clearance of niacin. The clinical relevance of this finding is unclear.

Bile Acid Sequestrants - An in vitro study was carried out investigating the niacin-binding capacity of colestipol and cholestyramine. About 98% of available niacin was bound to colestipol, with 10 to 30% binding to cholestyramine. These results suggest that 4 to 6 hours, or as great an interval as possible, should elapse between the ingestion of bile acid-binding resins and the administration of ADVICOR.

Other - Concomitant alcohol or hot drinks may increase the side effects of flushing and pruritus and should be avoided around the time of ADVICOR ingestion. Vitamins or other nutritional supplements containing large doses of niacin or related compounds such as nicotinamide may potentiate the adverse effects of ADVICOR.

Lovastatin

Lovastatin is metabolized by CYP3A4 but has no CYP3A4 inhibitory activity; therefore it is not expected to affect the plasma concentrations of other drugs metabolized by CYP3A4. Strong inhibitors of CYP3A4 (e.g., itraconazole, ketoconazole, posaconazole, clarithromycin, telithromycin, HIV protease inhibitors, boceprevir, telaprevir, nefazodone, and erythromycin), and large quantities of grapefruit juice (>1 quart daily) increase the risk of myopathy by reducing the elimination of lovastatin (see WARNINGS, Myopathy/Rhabdomyolysis).

In vitro studies have demonstrated that voriconazole inhibits the metabolism of lovastatin. Adjustment of the lovastatin dose may be needed to reduce the risk of myopathy, including rhabdomyolysis, if voriconazole must be used concomitantly with lovastatin.

Interactions With Lipid-Lowering Drugs That Can Cause Myopathy When Given Alone

The risk of myopathy is also increased by the following lipid-lowering drugs that are not strong CYP3A4 inhibitors, but which can cause myopathy when given alone (see WARNINGS, Myopathy/Rhabdomyolysis).

Gemfibrozil

Other fibrates

Other Drug Interactions

Cyclosporine: The risk of myopathy/rhabdomyolysis is increased by concomitant administration of cyclosporine (see WARNINGS, Myopathy/Rhabdomyolysis).

Danazol, Diltiazem, or Verapamil: The risk of myopathy/rhabdomyolysis is increased by concomitant administration of danazol, diltiazem, or verapamil particularly with higher doses of lovastatin (see WARNINGS, Myopathy/Rhabdomyolysis and CLINICAL PHARMACOLOGY, Pharmacokinetics).

Amiodarone: The risk of myopathy/rhabdomyolysis is increased when amiodarone is used concomitantly with a closely related member of the HMGCoA reductase inhibitor class (see WARNINGS, Myopathy/Rhabdomyolysis).

Coumarin Anticoagulants - In a small clinical study in which lovastatin was administered to warfarin-treated patients, no effect on PT was detected. However, another HMG-CoA reductase inhibitor has been found to produce a less than two seconds increase in PT in healthy volunteers receiving low doses of warfarin. Also, bleeding and/or increased PT have been reported in a few patients taking coumarin anticoagulants concomitantly with lovastatin. It is recommended that in patients taking anticoagulants, PT be determined before starting ADVICOR and frequently enough during early therapy to insure that no significant alteration of PT occurs. Once a stable PT has been documented, PT can be monitored at the intervals usually recommended for patients on coumarin anticoagulants. If the dose of ADVICOR is changed, the same procedure should be repeated.

Colchicine - Cases of myopathy, including rhabdomyolysis, have been reported with lovastatin coadministered with colchicine.

Ranolazine - The risk of myopathy, including rhabdomyolysis, may be increased by concomitant administration of ranolazine.

Propranolol - In normal volunteers, there was no clinically significant pharmacokinetic or pharmacodynamic interaction with concomitant administration of single doses of lovastatin and propranolol.

Digoxin - In patients with hypercholesterolemia, concomitant administration of lovastatin and digoxin resulted in no effect on digoxin plasma concentrations.

Oral Hypoglycemic Agents - In pharmacokinetic studies of lovastatin in hypercholesterolemic, non-insulin dependent diabetic patients, there was no drug interaction with glipizide or with chlorpropamide.

Drug/Laboratory Test Interactions

Niacin may produce false elevations in some fluorometric determinations of plasma or urinary catecholamines. Niacin may also give false-positive reactions with cupric sulfate solution (Benedict's reagent) in urine glucose tests.

Carcinogenesis, Mutagenesis, Impairment of Fertility

No studies have been conducted with ADVICOR regarding carcinogenesis, mutagenesis, or impairment of fertility.

Niacin

Niacin, administered to mice for a lifetime as a 1% solution in drinking water, was not carcinogenic. The mice in this study received approximately 6 to 8 times a human dose of 3000 mg/day as determined on a mg/m^2 basis. Niacin was negative for mutagenicity in the Ames test. No studies on impairment of fertility have been performed.

Lovastatin

In a 21-month carcinogenic study in mice, there was a statistically significant increase in the incidence of hepatocellular carcinomas and adenomas in both males and females at 500 mg/kg/day. This dose produced a total plasma drug exposure 3 to 4 times that of humans given the highest recommended dose of lovastatin (drug exposure was measured as total HMG-CoA reductase inhibitory activity in extracted plasma). Tumor increases were not seen at 20 and 100 mg/kg/day, doses that produced drug exposures of 0.3 to 2 times that of humans at the 80 mg/day dose. A statistically significant increase in pulmonary adenomas was seen in female mice at approximately 4 times the human drug exposure. (Although mice were given 300 times the human dose on a mg/kg body weight basis, plasma levels of total inhibitory activity were only 4 times higher in mice than in humans given 80 mg of lovastatin.)

There was an increase in incidence of papilloma in the non-glandular mucosa of the stomach of mice beginning at exposures of 1 to 2 times that of humans. The glandular mucosa was not affected. The human stomach contains only glandular mucosa.

In a 24-month carcinogenicity study in rats, there was a positive dose-response relationship for hepatocellular carcinogenicity in males at drug exposures between 2 to 7 times that of human exposure at 80 mg/day (doses in rats were 5, 30, and 180 mg/kg/day).

An increased incidence of thyroid neoplasms in rats appears to be a response that has been seen with other HMG-CoA reductase inhibitors.

A drug in this class chemically similar to lovastatin was administered to mice for 72 weeks at 25, 100, and 400 mg/kg body weight, which resulted in mean serum drug levels approximately 3, 15, and 33 times higher than the mean human serum drug concentration (as total inhibitory activity) after a 40 mg oral dose. Liver carcinomas were significantly increased in high-dose females and mid- and high-dose males, with a maximum incidence of 90% in males. The incidence of adenomas of the liver was significantly increased in mid- and high-dose females. Drug treatment also significantly increased the incidence of lung adenomas in mid- and high-dose males and females. Adenomas of the Harderian gland (a gland of the eye of rodents) were significantly higher in high-dose mice than in controls.

No evidence of mutagenicity was observed in a microbial mutagen test using mutant strains of Salmonella typhimurium with or without rat or mouse liver metabolic activation. In addition, no evidence of damage to genetic material was noted in an in vitro alkaline elution assay using rat or mouse hepatocytes, a V-79 mammalian cell forward mutation study, an in vitro chromosome aberration study in CHO cells, or an in vivo chromosomal aberration assay in mouse bone marrow.

Drug-related testicular atrophy, decreased spermatogenesis, spermatocytic degeneration and giant cell formation were seen in dogs starting at 20 mg/kg/day. Similar findings were seen with another drug in this class. No drug-related effects on fertility were found in studies with lovastatin in rats. However, in studies with a similar drug in this class, there was decreased fertility in male rats treated for 34 weeks at 25 mg/kg body weight, although this effect was not observed in a subsequent fertility study when this same dose was administered for 11 weeks (the entire cycle of spermatogenesis, including epididymal maturation). In rats treated with this same reductase inhibitor at 180 mg/kg/day, seminiferous tubule degeneration (necrosis and loss of spermatogenic epithelium) was observed. No microscopic changes were observed in the testes from rats of either study. The clinical significance of these findings is unclear.

Pregnancy

Pregnancy Category X

— See CONTRAINDICATIONS.

ADVICOR should be administered to women of childbearing potential only when such patients are highly unlikely to conceive and have been informed of the potential hazard. Safety in pregnant women has not been established and there is no apparent benefit to therapy with ADVICOR during pregnancy (see CONTRAINDICATIONS). Treatment should be immediately discontinued as soon as pregnancy is recognized.

Niacin

Animal reproduction studies have not been conducted with niacin or with ADVICOR. It is also not known whether niacin at doses typically used for lipid disorders can cause fetal harm when administered to pregnant women or whether it can affect reproductive capacity. If a woman receiving niacin or ADVICOR for primary hypercholesterolemia becomes pregnant, the drug should be discontinued.

Lovastatin

Rare reports of congenital anomalies have been received following intrauterine exposure to HMG-CoA reductase inhibitors. In a review^5 of approximately 100 prospectively followed pregnancies in women exposed to lovastatin or another structurally related HMG-CoA reductase inhibitor, the incidences of congenital anomalies, spontaneous abortions and fetal deaths/stillbirths did not exceed what would be expected in the general population. The number of cases is adequate only to exclude a 3- to 4-fold increase in congenital anomalies over the background incidence. In 89% of the prospectively followed pregnancies, drug treatment was initiated prior to pregnancy and was discontinued at some point in the first trimester when pregnancy was identified.

Lovastatin has been shown to produce skeletal malformations at plasma levels 40 times the human exposure (for mouse fetus) and 80 times the human exposure (for rat fetus) based on mg/m^2 surface area (doses were 800 mg/kg/day). No drug-induced changes were seen in either species at multiples of 8 times (rat) or 4 times (mouse) based on surface area. No evidence of malformations was noted in rabbits at exposures up to 3 times the human exposure (dose of 15 mg/kg/day, highest tolerated dose).

Labor and Delivery

No studies have been conducted on the effect of ADVICOR, niacin or lovastatin on the mother or the fetus during labor or delivery, on the duration of labor or delivery, or on the growth, development, and functional maturation of the child.

Nursing Mothers

No studies have been conducted with ADVICOR in nursing mothers.

Because of the potential for serious adverse reactions in nursing infants from lipid-altering doses of niacin and lovastatin (see CONTRAINDICATIONS), ADVICOR should not be taken while a woman is breastfeeding.

Niacin has been reported to be excreted in human milk. It is not known whether lovastatin is excreted in human milk. A small amount of another drug in this class is excreted in human breast milk.

Pediatric Use

No studies in patients under 18 years-of-age have been conducted with ADVICOR. Because pediatric patients are not likely to benefit from cholesterol lowering for at least a decade and because experience with this drug or its active ingredients is limited, treatment of pediatric patients with ADVICOR is not recommended at this time.

Geriatric Use

Of the 214 patients who received ADVICOR in double-blind clinical studies, 37.4% were 65 years-of-age and older, and of the 814 patients who received ADVICOR in open-label clinical studies, 36.2% were 65 years-of-age and older. Responses in LDL-C, HDL-C, and TG were similar in geriatric patients. No overall differences in the percentage of patients with adverse events were observed between older and younger patients. No overall differences were observed in selected chemistry values between the two groups except for amylase which was higher in older patients.

ADVERSE REACTIONS

Overview

In controlled clinical studies, 40/214 (19%) of patients randomized to ADVICOR discontinued therapy prior to study completion. Of the 214 patients enrolled 18 (8%) discontinued due to flushing. In the same controlled studies, 9/94 (10%) of patients randomized to lovastatin and 19/92 (21%) of patients randomized to NIASPAN also discontinued treatment prior to study completion secondary to adverse events. Flushing episodes (i.e., warmth, redness, itching and/or tingling) were the most common treatment-emergent adverse events, and occurred in 53% to 83% of patients treated with ADVICOR. Spontaneous reports with NIASPAN and clinical studies with ADVICOR suggest that flushing may also be accompanied by symptoms of dizziness or syncope, tachycardia, palpitations, shortness of breath, sweating, burning sensation/skin burning sensation, chills, and/or edema.

Adverse Reactions Information

Because clinical studies are conducted under widely varying conditions, adverse reaction rates observed in clinical studies of a drug cannot be directly compared to rates in the clinical studies of another drug and may not reflect the rates observed in clinical practice. The adverse reaction information from clinical studies does, however provide a basis for identifying the adverse events that appear to be related to drug use and for approximating rates.

The data described in this section reflect the exposure to ADVICOR in two double-blind, controlled clinical studies of 400 patients. The population was 28 to 86 years-of-age, 54% male, 85% Caucasian, 9% Black, and 7% Other, and had mixed dyslipidemia.

In addition to flushing, other adverse events occurring in 5% or greater of patients treated with ADVICOR are shown in Table 10 below.

Table 10. Treatment-Emergent Adverse Events in ≥ 5% of Patients (Events Irrespective of Causality; Data from Controlled, Double-Blind Studies)
Adverse Event | ADVICOR | NIASPAN | Lovastatin
Total Number of Patients | 214 | 92 | 94
Cardiovascular | 163 (76%) | 66 (72%) | 24 (26%)
Flushing | 152 (71%) | 60 (65%) | 17 (18%)
Body as a Whole | 104 (49%) | 50 (54%) | 42 (45%)
Asthenia | 10 (5%) | 6 (7%) | 5 (5%)
Flu Syndrome | 12 (6%) | 7 (8%) | 4 (4%)
Headache | 20 (9%) | 12 (13%) | 5 (5%)
Infection | 43 (20%) | 14 (15%) | 19 (20%)
Pain | 18 (8%) | 3 (3%) | 9 (10%)
Pain, Abdominal | 9 (4%) | 1 (1%) | 6 (6%)
Pain, Back | 10 (5%) | 5 (5%) | 5 (5%)
Digestive System | 51 (24%) | 26 (28%) | 16 (17%)
Diarrhea | 13 (6%) | 8 (9%) | 2 (2%)
Dyspepsia | 6 (3%) | 5 (5%) | 4 (4%)
Nausea | 14 (7%) | 11 (12%) | 2 (2%)
Vomiting | 7 (3%) | 5 (5%) | 0
Metabolic and Nutrit. System | 37 (17%) | 18 (20%) | 13 (14%)
Hyperglycemia | 8 (4%) | 6 (7%) | 6 (6%)
Musculoskeletal System | 19 (9%) | 9 (10%) | 17 (18%)
Myalgia | 6 (3%) | 5 (5%) | 8 (9%)
Skin and Appendages | 38 (18%) | 19 (21%) | 11 (12%)
Pruritus | 14 (7%) | 7 (8%) | 3 (3%)
Rash | 11 (5%) | 11 (12%) | 3 (3%)
Note: Percentages are calculated from the total number of patients in each column.

See also the full prescribing information for niacin extended release (Niaspan) and lovastatin products.

The following adverse events have also been reported with niacin, lovastatin, and/or other HMG-CoA reductase inhibitors, but not necessarily with ADVICOR, either during clinical studies or in routine patient management.

Body as a Whole: | chest pain; abdominal pain; edema; chills; malaise
Cardiovascular: | atrial fibrillation; tachycardia; palpitations, and other cardiac arrhythmias; postural hypotension, orthostasis; hypotension; syncope
Eye: | toxic amblyopia; cystoid macular edema; ophthalmoplegia; eye irritation, blurred vision, progression of cataracts
Gastrointestinal: | activation of peptic ulcers and peptic ulceration; dyspepsia; vomiting; anorexia; constipation; flatulence, pancreatitis; hepatitis; fatty change in liver; jaundice; and rarely, cirrhosis, fulminant hepatic necrosis, and hepatoma, eructation, fatal and non-fatal hepatic failure
Metabolic: | gout, decreased glucose tolerance
Musculoskeletal: | muscle cramps; myopathy; rhabdomyolysis; arthralgia, myalgia
Nervous: | dizziness; insomnia; dry mouth; paresthesia; anxiety; tremor; vertigo; peripheral neuropathy; psychic disturbances; dysfunction of certain cranial nerves, nervousness, burning sensation/skin burning sensation, peripheral nerve palsy
Psychiatric | depression
Skin: | hyper-pigmentation; acanthosis nigricans; urticaria; alopecia; dry skin; sweating; and a variety of skin changes (e.g., nodules, discoloration, dryness of mucous membranes, changes to hair/nails), vesiculobullous rash, maculopapular rash
Respiratory: | dyspnea; rhinitis
Urogenital: | gynecomastia; loss of libido; erectile dysfunction
Hypersensitivity reactions: | An apparent hypersensitivity syndrome has been reported rarely, which has included one or more of the following features: anaphylaxis, angioedema, tongue edema, larynx edema, face edema, peripheral edema, laryngismus, lupus erythematous-like syndrome, polymyalgia rheumatica, vasculitis, purpura, thrombocytopenia, leukopenia, hemolytic anemia, positive ANA, ESR increase, eosinophilia, arthritis, arthralgia, urticaria, asthenia, photosensitivity, fever, chills, flushing, malaise, dyspnea, toxic epidermal necrolysis, erythema multiforme, including Stevens-Johnson syndrome, dermatomyositis
Other: | migraine

There have been rare postmarketing reports of cognitive impairment (e.g., memory loss, forgetfulness, amnesia, memory impairment, confusion) associated with statin use. These cognitive issues have been reported for all statins. The reports are generally nonserious, and reversible upon statin discontinuation, with variable times to symptom onset (1 day to years) and symptom resolution (median of 3 weeks).

Clinical Laboratory Abnormalities

Chemistry

Elevations in serum transaminases (see WARNINGS - Liver Dysfunction), CPK and fasting glucose, and reductions in phosphorus. Niacin extended-release tablets have been associated with slight elevations in LDH, uric acid, total bilirubin, amylase and creatine kinase. Lovastatin and/or HMG-CoA reductase inhibitors have been associated with elevations in alkaline phosphatase, γ-glutamyl transpeptidase and bilirubin, and thyroid function abnormalities.

Hematology

Niacin extended-release tablets have been associated with slight reductions in platelet counts and prolongation in PT (see WARNINGS).

DRUG ABUSE AND DEPENDENCE

Neither niacin nor lovastatin is a narcotic drug. ADVICOR has no known addiction potential in humans.

OVERDOSAGE

Information on acute overdose with ADVICOR in humans is limited. Until further experience is obtained, no specific treatment of overdose with ADVICOR can be recommended. The patient should be carefully observed and given supportive treatment.

Niacin

The s.c. LD50 of niacin is 5 g/kg in rats.

The signs and symptoms of an acute overdose of niacin can be anticipated to be those of excessive pharmacologic effect: severe flushing, nausea/vomiting, diarrhea, dyspepsia, dizziness, syncope, hypotension, possibly cardiac arrhythmias and clinical laboratory abnormalities. Insufficient information is available on the potential for the dialyzability of niacin.

Lovastatin

After oral administration of lovastatin to mice the median lethal dose observed was >15 g/m^2.

Five healthy human volunteers have received up to 200 mg of lovastatin as a single dose without clinically significant adverse experiences. A few cases of accidental overdose have been reported; no patients had any specific symptoms, and all patients recovered without sequelae. The maximum dose taken was 5 to 6 g. The dialyzability of lovastatin and its metabolites in man is not known at present.

DOSAGE AND ADMINISTRATION

The patient should be placed on a standard cholesterol-lowering diet before receiving ADVICOR or its individual active components and should continue on this diet during treatment with lipid-altering therapy (see NCEP Treatment Guidelines for details on dietary therapy).

ADVICOR

ADVICOR should be taken at bedtime, with a low-fat snack. ADVICOR tablets should be taken whole and should not be broken, crushed, or chewed before swallowing. Patients not currently on NIASPAN must start ADVICOR at the lowest initial ADVICOR dose, a single 500 mg/20 mg tablet once daily at bedtime. The dose of ADVICOR should not be increased by more than 500 mg daily (based on the NIASPAN component) every 4 weeks. The dose of ADVICOR should be individualized based on targeted goals for cholesterol and triglycerides, and on patient response. Doses of ADVICOR greater than 2000 mg/40 mg daily are not recommended. If ADVICOR therapy is discontinued for an extended period (>7 days), reinstitution of therapy should begin with the lowest dose of ADVICOR.

Flushing of the skin (see ADVERSE REACTIONS) may be reduced in frequency or severity by pretreatment with aspirin up to the recommended dose of 325 mg (taken up to approximately 30 minutes prior to ADVICOR dose). Flushing, pruritus, and gastrointestinal distress are also greatly reduced by slowly increasing the dose of niacin and avoiding administration on an empty stomach.

Equivalent doses of ADVICOR may be substituted for equivalent doses of NIASPAN but should not be substituted for other modified-release (sustained-release or time-release) niacin preparations or immediate-release (crystalline) niacin preparations (see WARNINGS). Patients previously receiving niacin products other than NIASPAN should be started on NIASPAN with the recommended NIASPAN titration schedule, and the dose should subsequently be individualized based on patient response. A relative bioavailability study results indicated that ADVICOR tablet strengths (i.e. two tablets of 500 mg/20 mg and one tablet of 1000 mg/40 mg) are not interchangeable.

NIASPAN

NIASPAN should be taken at bedtime, after a low-fat snack, and doses should be individualized according to patient response. Therapy with NIASPAN must be initiated at 500mg at bedtime in order to reduce the incidence and severity of side effects which may occur during early therapy. NIASPAN must be titrated and the dose should not be increased by more than 500 mg every 4 weeks up to a maximum dose of 2000 mg a day. The recommended dose escalation is shown in Table 11 below. Patients already receiving a stable dose of NIASPAN may be switched directly to a niacin-equivalent dose of ADVICOR.

Table 11. Recommended Dosing

Maintenance Dose:

The daily dosage of NIASPAN should not be increased by more than 500 mg in any 4-week period. The recommended maintenance dose is 1000 mg (two 500 mg tablets) to 2000 mg (two 1000 mg tablets or four 500 mg tablets) once daily at bedtime. Doses greater than 2000 mg daily are not recommended. Women may respond at lower NIASPAN doses than men.

Flushing of the skin (see ADVERSE REACTIONS) may be reduced in frequency or severity by pretreatment with aspirin up to the recommended dose of 325 mg (taken 30 minutes prior to NIASPAN dose). Tolerance to this flushing develops rapidly over the course of several weeks. Flushing, pruritus, and gastrointestinal distress are also greatly reduced by slowly increasing the dose of niacin and avoiding administration on an empty stomach. Concomitant alcoholic, hot drinks or spicy foods may increase the side effects of flushing and pruritus and should be avoided around the time of ADVICOR ingestion.

Equivalent doses of NIASPAN should not be substituted for sustained-release (modified-release, timed-release) niacin preparations or immediate-release (crystalline) niacin (see WARNINGS). Patients previously receiving other niacin products should be started with the recommended NIASPAN titration schedule (see Table 11), and the dose should subsequently be individualized based on patient response. Single-dose bioavailability studies have demonstrated that NIASPAN tablet strengths are not interchangeable.

If NIASPAN therapy is discontinued for an extended period, reinstitution of therapy should include a titration phase (see Table 11).

NIASPAN tablets should be taken whole and should not be broken, crushed or chewed before swallowing.

Concomitant Therapy

Concomitant Therapy with Lovastatin

Patients already receiving a stable dose of lovastatin who require further TG-lowering or HDL-raising (e.g., to achieve NCEP non-HDL-C goals), may receive concomitant dosage titration with NIASPAN per NIASPAN recommended initial titration schedule (see Table 10, DOSAGE AND ADMINISTRATION section). For patients already receiving a stable dose of NIASPAN who require further LDL-lowering (e.g., to achieve NCEP LDL-C goals; Table 8), the usual recommended starting dose of lovastatin is 20 mg once a day. Dose adjustments should be made at intervals of 4 weeks or more. Combination therapy with NIASPAN and lovastatin should not exceed doses of 2000 mg and 40 mg daily, respectively.

Dosage in Patients with Renal or Hepatic Insufficiency

Use of NIASPAN in patients with renal or hepatic insufficiency has not been studied. NIASPAN is contraindicated in patients with significant or unexplained hepatic dysfunction (see WARNINGS, PRECAUTIONS. NIASPAN should be used with caution in patients with renal insufficiency (see CLINICAL PHARMACOLOGY).

Lovastatin

The usual recommended starting dose is 20 mg once a day given with the evening meal. The recommended dosing range is 10-80 mg/day in single or two divided doses; the maximum recommended dose is 80 mg/day. Doses should be individualized according to the recommended goal of therapy (see NCEP Guidelines and CLINICAL PHARMACOLOGY). Patients requiring reductions in LDL cholesterol of 20% or more to achieve their goal (see INDICATIONS AND USAGE) should be started on 20 mg/day of lovastatin. A starting dose of 10 mg may be considered for patients requiring smaller reductions. Adjustments should be made at intervals of 4 weeks or more.

Cholesterol levels should be monitored periodically and consideration should be given to reducing the dosage of lovastatin if cholesterol levels fall significantly below the targeted range.

Dosage in Patients taking Danazol, Diltiazem or Verapamil

In patients taking danazol, diltiazem, or verapamil concomitantly with lovastatin (see WARNINGS, Myopathy/Rhabdomyolysis), therapy should begin with 10 mg of lovastatin and should not exceed 20 mg/day.

Dosage in Patients taking Amiodarone

In patients taking amiodarone concomitantly with lovastatin, the dose should not exceed 40 mg/day (see WARNINGS, Myopathy/Rhabdomyolysis and PRECAUTIONS, Drug Interactions, Other drug interactions).

Concomitant Lipid-Lowering Therapy

Use of lovastatin with gemfibrozil should be avoided.

Caution should be used when prescribing other fibrates with lovastatin, as fibrates can cause myopathy when given alone.

Dosage in Patients with Renal Insufficiency

In patients with severe renal insufficiency (creatinine clearance <30 mL/min), dosage increases above 20 mg/day should be carefully considered and, if deemed necessary, implemented cautiously (see CLINICAL PHARMACOLOGY and WARNINGS, Myopathy/Rhabdomyolysis).

HOW SUPPLIED

ADVICOR is an unscored capsule-shaped tablet containing either 500, 750, or 1000 mg of extended-release niacin, and 20 mg of immediate-release lovastatin (ADVICOR 500 mg/20 mg, 750 mg/20 mg, 1000 mg/20 mg), or 1000 mg of extended-release niacin and 40 mg of immediate-release lovastatin (ADVICOR 1000 mg/40 mg). Tablets are color-coated and printed with the Abbott ‘A’ logo and a code number specific to the tablet strength on the same side. ADVICOR 500 mg/20 mg tablets are light yellow, code “502”. ADVICOR 750 mg/20 mg tablets are light orange, code “752”. ADVICOR 1000 mg/20 mg tablets are dark pink/light purple, code “1002”. ADVICOR 1000 mg/40 mg tablets are reddish brown, code “1004.” Tablets are supplied in bottles of 90 tablets as shown below.

500 mg/20 mg tablets:

bottles of 30 - NDC 54868-4807-1

bottles of 60 - NDC 54868-4807-0

1000 mg/40 mg tablets:

bottles of 30 - NDC 54868-5653-0

bottles of 90 - NDC 54868-5653-1

Store at room temperature (20° to 25°C or 68° to 77°F).

NIASPAN is a registered trademark of Abbott Laboratories, and Mevacor is a registered trademark of Merck & Co., Inc.

REFERENCES

1. Executive Summary of the Third Report of the National Cholesterol Education Program (NCEP) Expert Panel on Detection, Evaluation, and Treatment of High Blood Cholesterol in Adults (Adult Treatment Panel III). JAMA 2001; 285:2486-2497.
2. Downs JR, et al. JAMA 1998; 279:1615-1622.
3. Bradford RH, et al. Arch Intern Med 1991;151:43-49.
4. Bradford RH, et al. Am J Cardiol 1994; 74:667-673.
5. Manson JM, et al. Reprod Toxicol 1996; 10(6): 439-446.

Manufactured by Abbott Pharmaceuticals PR Ltd., Barceloneta, PR 00617
for Abbott Laboratories, North Chicago, IL 60064, U.S.A.

© 2012 Abbott Laboratories

Revised: 04/2012

Relabeling and Repackaging by:
Physicians Total Care, Inc.
Tulsa, Oklahoma 74146

PACKAGE LABEL

Advicor®

Niacin Extended-Release/Lovastatin

500 mg / 20 mg

Rx only

Advicor®

Niacin Extended-Release/Lovastatin

1000 mg / 20 mg

Rx only

Advicor®

Niacin Extended-Release/Lovastatin

1000 mg / 40 mg

Rx only